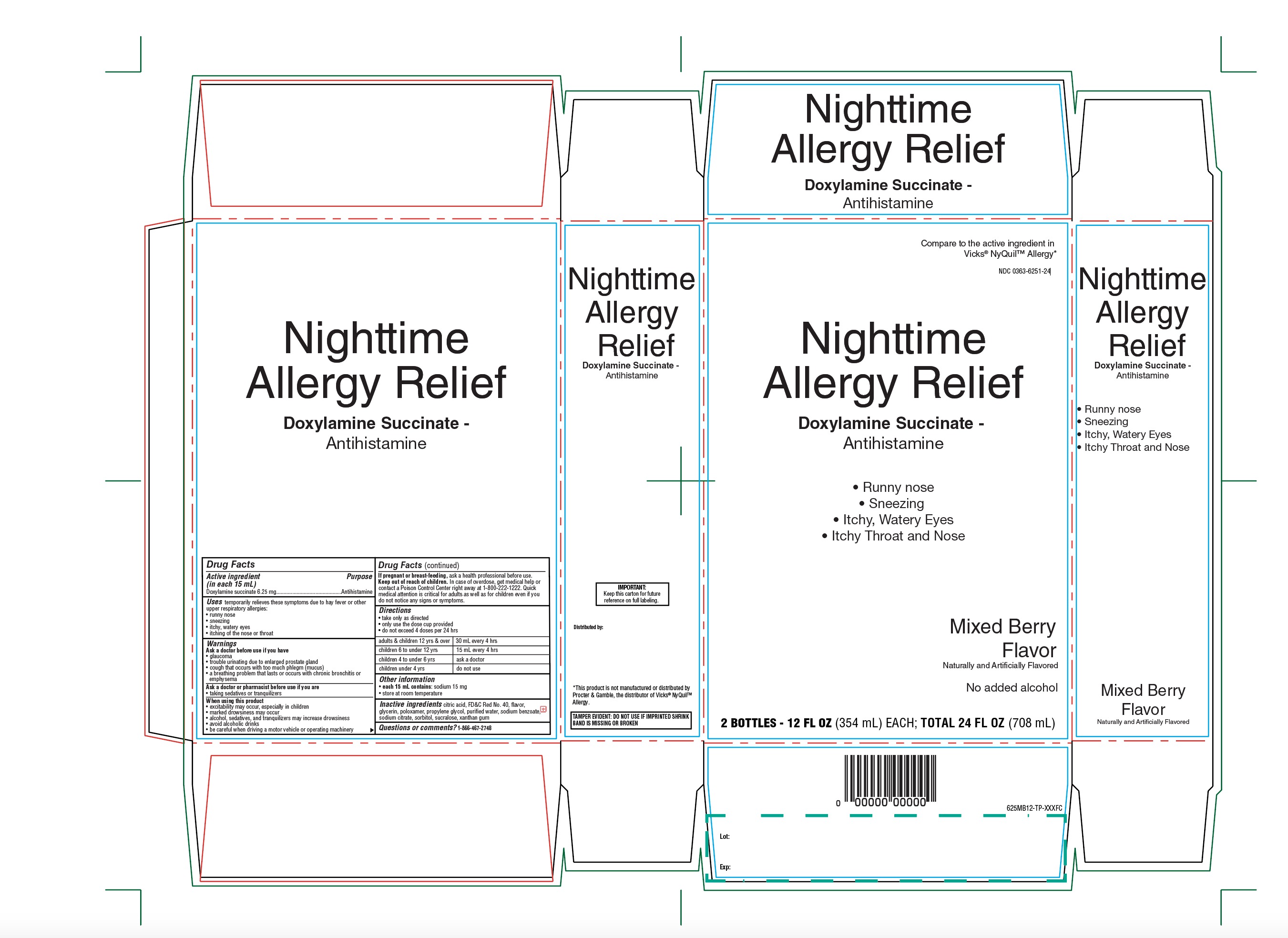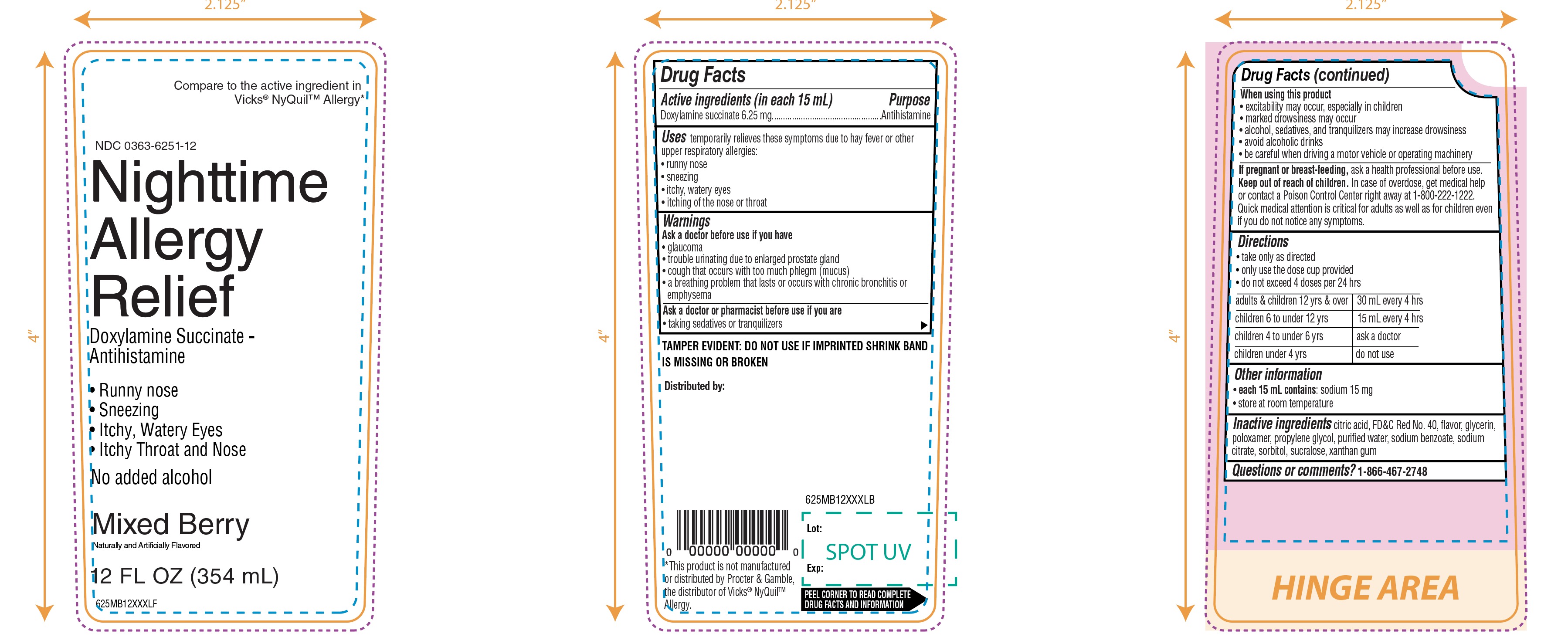 DRUG LABEL: WALGREENS

NDC: 0363-6251 | Form: LIQUID
Manufacturer: WALGREENS CO.
Category: otc | Type: HUMAN OTC DRUG LABEL
Date: 20260227

ACTIVE INGREDIENTS: DOXYLAMINE SUCCINATE 6.25 mg/15 mL
INACTIVE INGREDIENTS: ANHYDROUS CITRIC ACID; FD&C RED NO. 40; GLYCERIN; POLOXAMER 124; PROPYLENE GLYCOL; WATER; SODIUM BENZOATE; TRISODIUM CITRATE DIHYDRATE; SORBITOL; SUCRALOSE; XANTHAN GUM

Walgreen Nighttime Allergy Relief

Drug Facts

Active ingredient (in each 15 mL)

Doxylamine succinate 6.25 mg

Purpose

Antihistamine

Uses

temporarily relieves these symptoms due to hay fever or other upper respiratory allergies:

- runny nose
- sneezing
- itchy, watery eyes
- itching of the nose or throat

Ask a doctor before use if you have

- glaucoma
- trouble urinating due to enlarged prostate gland
- cough that occurs with too much phlegm (mucus)
- a breathing problem that lasts or occurs with chronic bronchitis or emphysema

Ask a doctor or pharmacist before use if you are

- taking sedatives or tranquilizers.

When using this product

- excitability may occur, especially in children
- marked drowsiness may occur
- alcohol, sedatives, and tranquilizers may increase drowsiness
- avoid alcoholic drinks
- be careful when driving a motor vehicle or operating machinery

If pregnant or breast-feeding,

ask a health professional before use.

OVERDOSAGE

In case of overdose, get medical help or contact a Poison Control Center right away at 1-800-222-1222. Quick medical attention is critical for adults as well as for children even if you do not notice any signs or symptoms.

Directions

- take only as directed
- only use the dose cup provided
- do not exceed 4 doses per 24 hrs

adults & children 12 yrs & over | 30 mL every 4 hrs
children 6 to under 12 yrs | 15 mL every 4 hrs
children 4 to under 6 yrs | ask a doctor
children under 4 yrs | do not use

Other information

- each 15 mL contains:sodium 15 mg
- Store at room temperature

Inactive ingredients

citric acid, FD&C Red No. 40, flavor, glycerin, poloxamer, propylene glycol, glycol, purified water, sodium benzoate, sodium citrate, sorbitol, sucralose, xanthan gum

Questions or comments?

1-866-467-2748

TAMPER EVIDENT: DO NOT USE IF IMPRINTED SHRINKBAND IS MISSING OR BROKEN.

Distributed by:

PRINCIPAL DISPLAY PANEL

Compare to the active ingredient in Vicks® NyQuil™ Allergy*

NDC 0363-6251-24

Nighttime

Allergy Relief

Doxylamine Succinate -Antihistamine

- Runny Nose
- Sneezing
- Itchy, Watery Eyes
- Itchy Throat and Nose

Mixed Berry Flavor

Naturally and Artificially Flavored

2 BOTTLES -12 FL OZ (354 mL) EACH; TOTAL 24 FL OZ(708 ML)

*This product is not manufactured or distributed by Procter & Gamble, the distributor of Vicks® NyQuil™ Allergy.